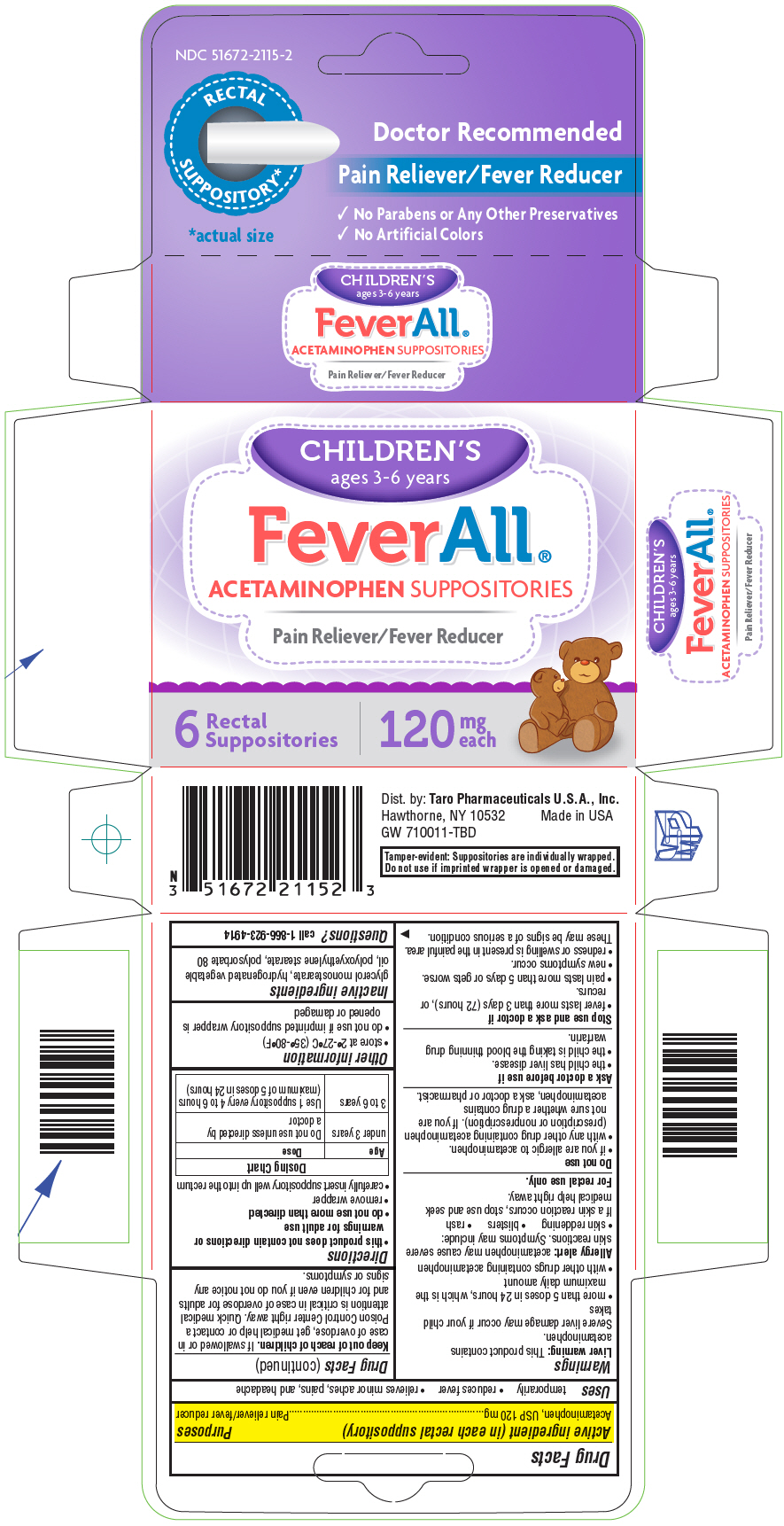 DRUG LABEL: Feverall 


NDC: 51672-2115 | Form: SUPPOSITORY
Manufacturer: Sun Pharmaceutical Industries, Inc.
Category: otc | Type: HUMAN OTC DRUG LABEL
Date: 20260202

ACTIVE INGREDIENTS: ACETAMINOPHEN 120 mg/1 1
INACTIVE INGREDIENTS: GLYCERYL MONOSTEARATE; HYDROGENATED PALM KERNEL OIL; PEG-100 STEARATE; POLYSORBATE 80

Feverall®
Children's

Drug Facts

Active ingredient (in each rectal suppository)

Acetaminophen, USP 120 mg

Purposes

Pain reliever/fever reducer

Uses

temporarily

- reduces fever
- relieves minor aches, pains, and headache

Warnings

Liver warning

This product contains acetaminophen.

Severe liver damage may occur if your child takes

- more than 5 doses in 24 hours, which is the maximum daily amount
- with other drugs containing acetaminophen

Allergy alert:acetaminophen may cause severe skin reactions. Symptoms may include:

- skin reddening
- blisters
- rash

If a skin reaction occurs, stop use and seek medical help right away.

For rectal use only.

Do not use

- if you are allergic to acetaminophen.
- with any other drug containing acetaminophen (prescription or nonprescription). If you are not sure whether a drug contains acetaminophen, ask a doctor or pharmacist.

Ask a doctor before use if

- the child has liver disease.
- the child is taking the blood thinning drug warfarin.

Stop use and ask a doctor if

- fever lasts more than 3 days (72 hours), or recurs.
- pain lasts more than 5 days or gets worse.
- new symptoms occur.
- redness or swelling is present in the painful area.

These may be signs of a serious condition.

Keep out of reach of children.If swallowed or in case of overdose, get medical help or contact a Poison Control Center right away. Quick medical attention is critical in case of overdose for adults and for children even if you do not notice any signs or symptoms.

Directions

- this product does not contain directions or warnings for adult use
- do not use more than directed
- remove wrapper
- carefully insert suppository well up into the rectum

Dosing Chart
Age | Dose
under 3 years | Do not use unless directed by a doctor
3 to 6 years | Use 1 suppository every 4 to 6 hours (maximum of 5 doses in 24 hours)

Other information

- store at 2°-27°C (35°-80°F)
- do not use if imprinted suppository wrapper is opened or damaged

Inactive ingredients

glycerol monostearate, hydrogenated vegetable oil, polyoxyethylene stearate, polysorbate 80

Questions?

call 1-866-923-4914

Dist. by: Taro Pharmaceuticals U.S.A., Inc.
Hawthorne, NY 10532

PRINCIPAL DISPLAY PANEL - 120 mg Suppository Blister Pack Carton

NDC 51672-2115-2

RECTAL
SUPPOSITORY*

*actual size

Doctor Recommended

Pain Reliever/Fever Reducer

- No Parabens or Any Other Preservatives
- No Artificial Colors

CHILDREN'S

ages 3-6 years

FeverAll®

ACETAMINOPHEN SUPPOSITORIES

Pain Reliever/Fever Reducer

6
Rectal
Suppositories

120
mg
each